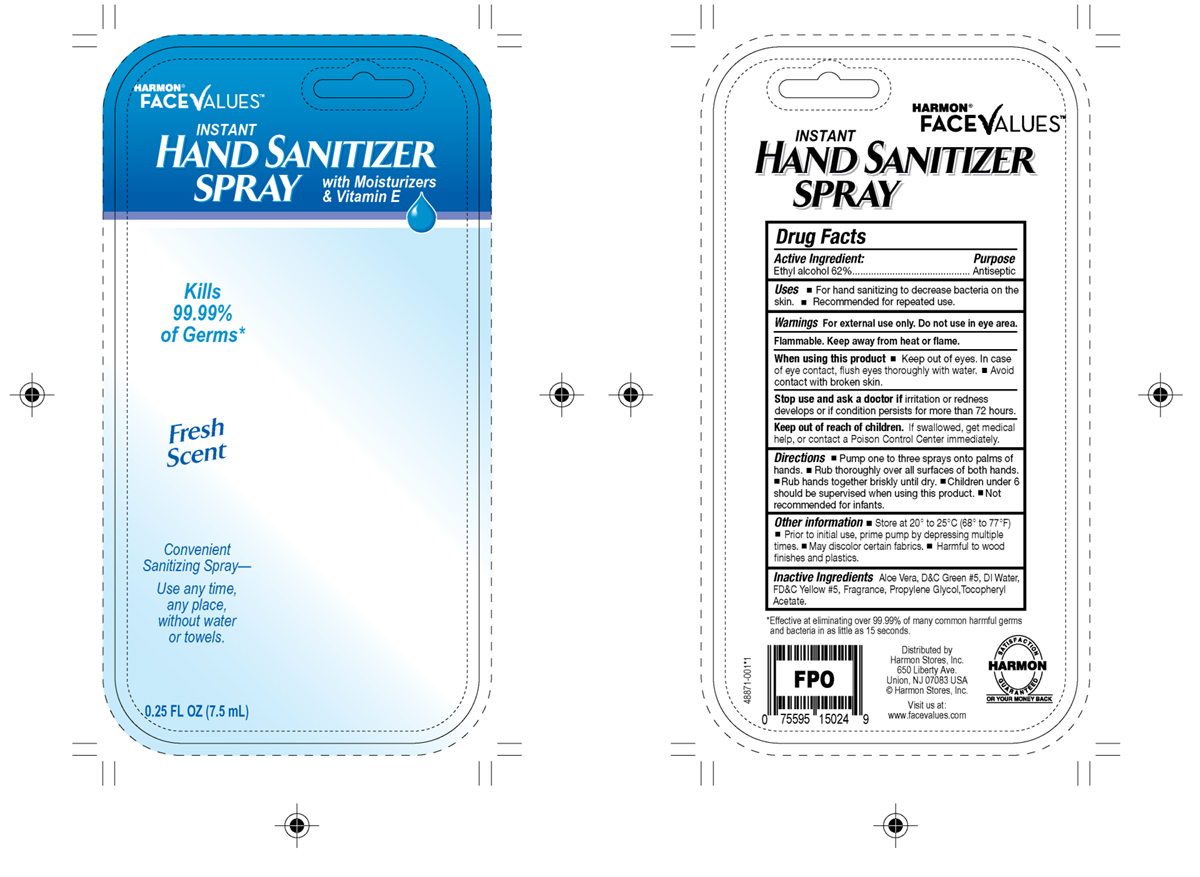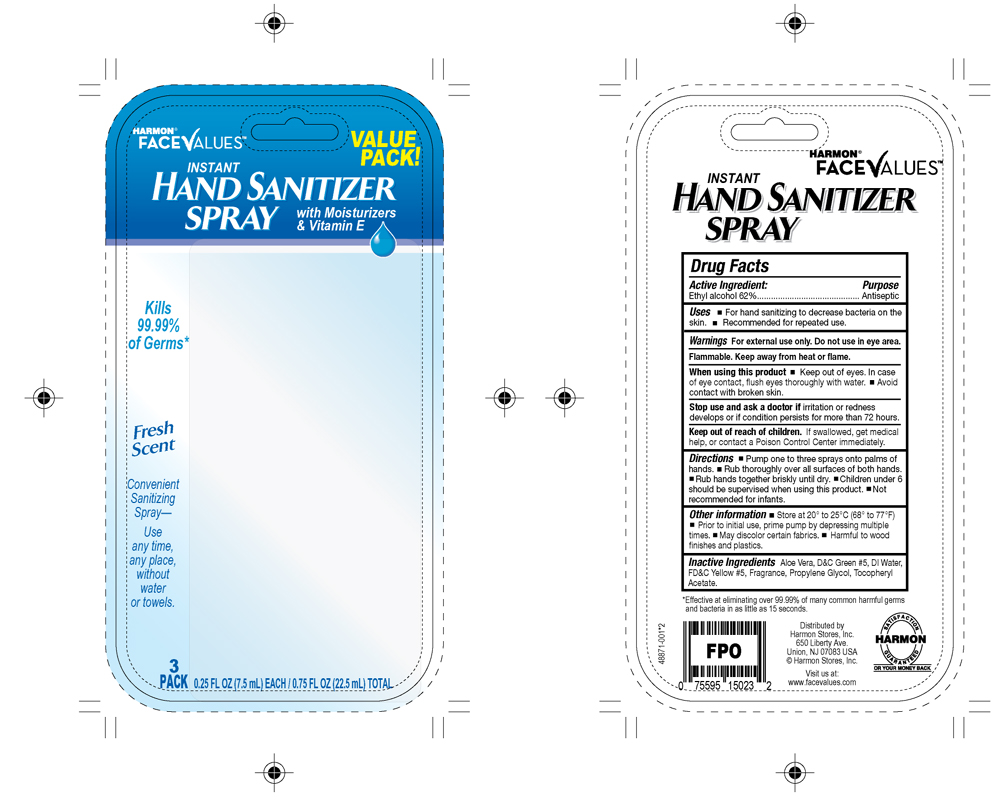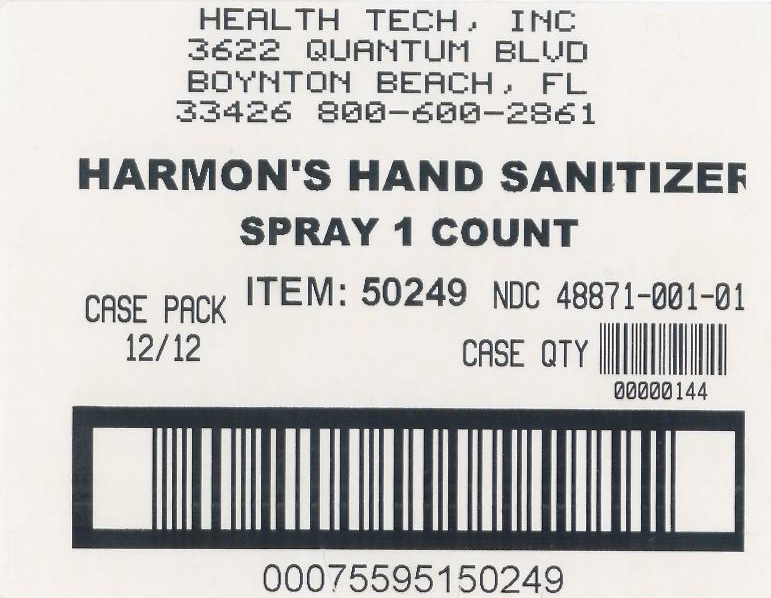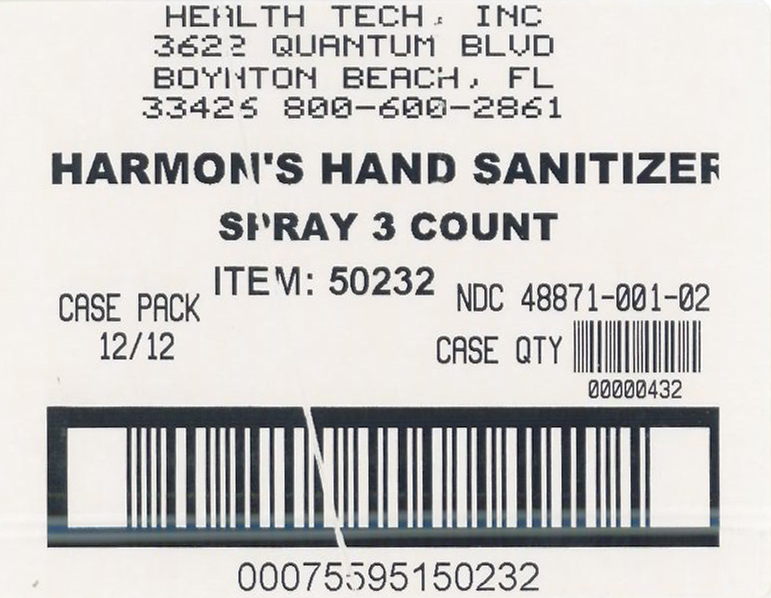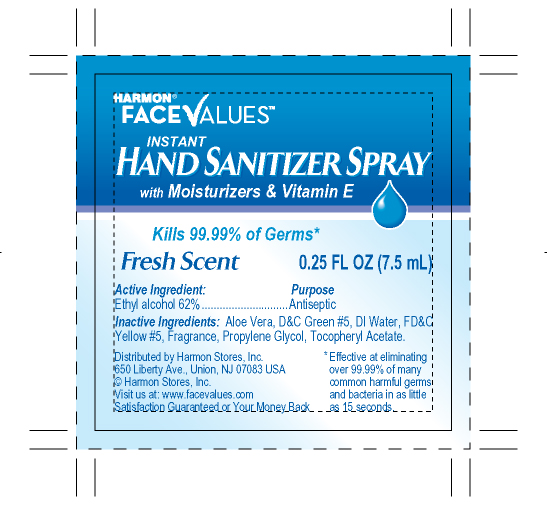 DRUG LABEL: Harmon Face Values
NDC: 48871-001 | Form: SPRAY
Manufacturer: Health-Tech, Inc.
Category: otc | Type: HUMAN OTC DRUG LABEL
Date: 20100222

ACTIVE INGREDIENTS: Ethanol 4.65 mL/7.5 mL
INACTIVE INGREDIENTS: aloe vera leaf; Propylene glycol; ALPHA-TOCOPHEROL ACETATE; Water

Drug Facts

Active Ingredients

Ethanol

PURPOSE

Antiseptic

Uses

- For hand sanitizing to decrease bacteria on the skin
- Recommended for repeated use

Warnings

- For external use only
- Do not use in eye are

Flammable: Keep away from heat or flame

When using this product

- Keep out of eyes. In case of eye contact, flush eyes thoroughly with water.
- Avoid contact with broken skin.

Stop use and ask a doctor if

Irritation or redness develops or if condition persists for more than 72 hours.

Keep out of reach of Children

If swallowed, get medical help, or contact a Poison Control Center immediately.

Directions

- Pump one to three sprays onto palms of hands
- Rub thoroughly over all surfaces of both hands
- Rub hands together briskly until dry
- Children under 6 should be supervised when using this product
- Not recommended for infants

Other Information

- Store at 20^0 to 25^0 C (68^0 to 77^0 F)
- Prior to initial use, prime pump by depressing multiple times
- May discolor certain fabrics
- Harmful to wood finishes and plastics

Inactive Ingredients

Aloe Vera, D and C Green 5, DI Water, FD and C Yellow 5, Fragrance, Propylene Glycol, Tocopheryl Acetate

PACKAGE LABEL

MM4

PACKAGE LABEL

MM5

PACKAGE LABEL

MM6

PACKAGE LABEL

MM7

PACKAGE LABEL

MM8